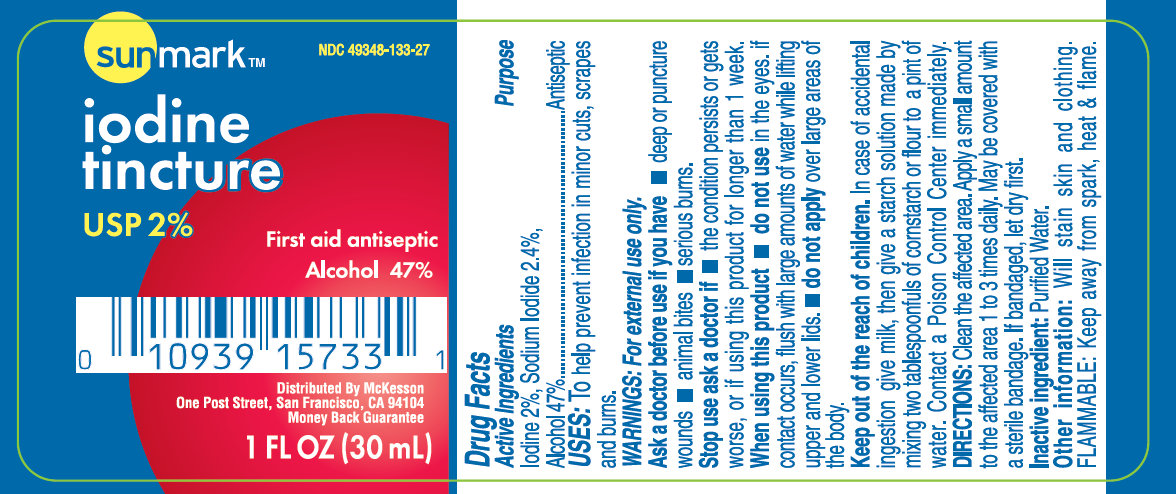 DRUG LABEL: Sunmark Iodine
NDC: 49348-133 | Form: TINCTURE
Manufacturer: Strategic Sourcing Services LLC
Category: otc | Type: HUMAN OTC DRUG LABEL
Date: 20231219

ACTIVE INGREDIENTS: IODINE 20 mg/1 mL; ALCOHOL 470 mg/1 mL; SODIUM IODIDE 24 mg/1 mL
INACTIVE INGREDIENTS: WATER

Sunmark Iodine Tincture USP 2%

Active Ingredients

Iodine 2%, Sodium Iodide 2.4%, Alcohol 47%

Purpose

Antiseptic

Uses

To help prevent infection in minor cuts, scrapes and burns.

WARNINGS:

For external use only.

DIRECTIONS:

Clean the affected area. Apply a small amount to the affected area 1 to 3 times daily. May be covered with a sterile bandage. If bandaged, let dry first.

Inactive ingredient:

Purified Water.

KEEP OUT OF REACH OF CHILDREN

In case of accidental ingestion, seek professional assistance or contact a Poison Control Center immediately.